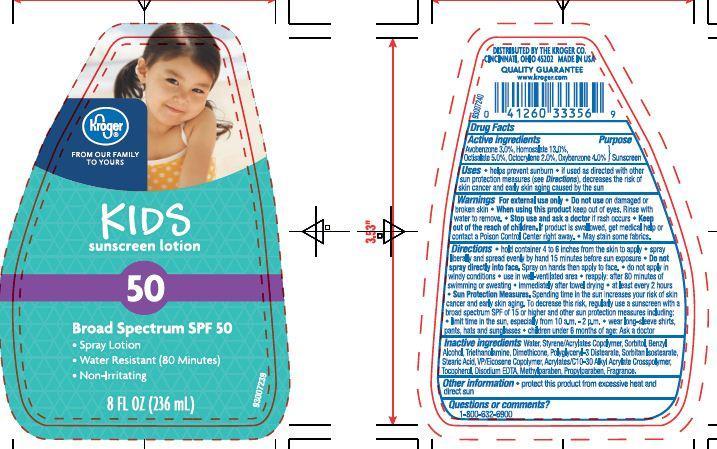 DRUG LABEL: Kroger Kroger Kids Sunscreen
NDC: 30142-920 | Form: SPRAY
Manufacturer: THE KROGER CO
Category: otc | Type: HUMAN OTC DRUG LABEL
Date: 20130911

ACTIVE INGREDIENTS: AVOBENZONE 3 g/100 g; HOMOSALATE 13 g/100 g; OCTISALATE 5 g/100 g; OCTOCRYLENE 2 g/100 g; OXYBENZONE 4 g/100 g
INACTIVE INGREDIENTS: DIMETHICONE; SORBITOL; TROLAMINE; STEARIC ACID; BENZYL ALCOHOL; SORBITAN ISOSTEARATE; METHYLPARABEN; PROPYLPARABEN; TOCOPHEROL; EDETATE DISODIUM; WATER; POLYGLYCERYL-3 DISTEARATE

Drug Facts

Active ingredients

Avobenzone 3.0 %

Homosalate 13.0%

Octisalate 5.0%

Octocrylene 2.0%

Oxybenzone 4.0%

Purpose

Sunscreen

Uses

- Helps prevent sunburn
- If used as directed with other sun protection measures (see Directions), decrease the risk of skin cancer and early skin aging caused by the sun.

Warnings

For external use only. Do not use on damaged or broken skin.

When using this product

keep out of eyes. Rinse with water to remove.

Stop use and ask a doctor if

rash occurs.

Keep out of the reach of children

If swallowed, get medical help or contact a Poison Control Center right away.

Directions

- hold container 4-6 inches from the skin to apply
- spray liberally and spread evenly by hand 15 minutes before sun exposure
- Do not spray directly on face. Spray on hands and then apply to face
- do not apply in windy conditions
- use in well ventilated area
- reapply
- after 80 minutes of swimming or sweating
- immediately after towel drying
- at least every 2 hours
- Sun Protection Measures: Spending time in the sun increases your risk of skin cancer and early skin aging. To decrease this risk, regularly use a sunscreen with a broad spectrum SPF of 15 or higher and other sun protection measures including:
- limit time in the sun, especially from 10 a.m. - 2 p.m.
- wear long-sleeve shirts, pants, hats and sunglasses
- children under 6 months of age: Ask a doctor

Other Information

- protect this product form excessive heat and direct sun

Inactive Ingredients

Water, Styrene/Acrylates Copolymer, Sorbitol, Benzyl Alcohol, Triethanolamine, Dimethicone, Polyglyceryl-3 Distearate, Sorbitan Isostearate, Stearic Acid, VP/Eicosene Copolymer, Acrylates/C10-30 Alkyl Acrylate Crosspolymer, Tocopherol, Disodium EDTA, Methylparaben, Propylparaben, Fragrance.

Principal Display Panel

Kroger

FROM OUR FAMILY TO YOURS

KIDS

sunscreen lotion

50

Broad Spectrum SPF 50

Spray Lotion

Water Resistant (80 Minutes)

Non-Irritating

8 FL OZ (236 mL)

Questions or comments?

1-800-632-6900